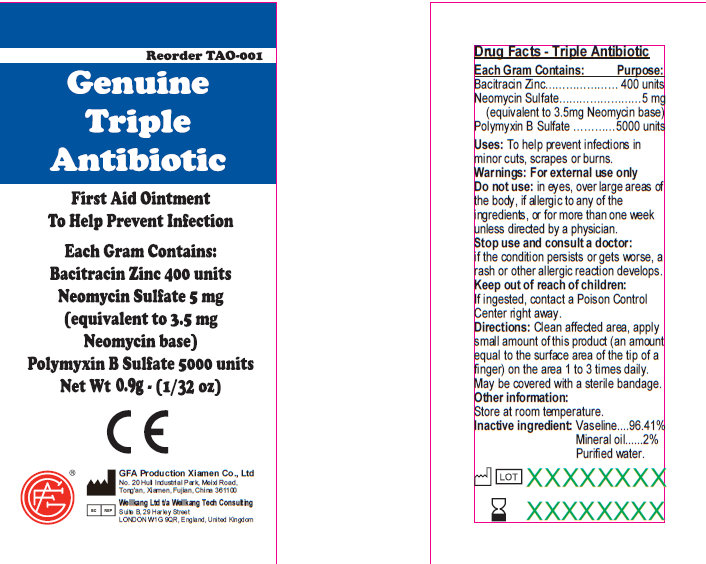 DRUG LABEL: Genuine Triple Antibiotic
                        
NDC: 52124-0003 | Form: OINTMENT
Manufacturer: Genuine First Aid LLC
Category: otc | Type: HUMAN OTC DRUG LABEL
Date: 20120425

ACTIVE INGREDIENTS: BACITRACIN ZINC 400 [iU]/1 g; NEOMYCIN SULFATE 5 mg/1 g; POLYMYXIN B SULFATE 5000 [iU]/1 g
INACTIVE INGREDIENTS: PETROLATUM; MINERAL OIL; WATER

Genuine Triple Antibiotic

Active Ingredients

Active Ingredient: .........Bacitracin Zinc 400 units

Neomycin Sulfate 5mg (equivalent to 3.5 mg Neomycin base)

Polymyxin B Sulfate 5000 units

Purpose

Triple Antibiotic

INDICATIONS AND USAGE

Uses: To help prevent infection in:
minor cuts; scrapes; burns

Warnings

For external use only.

Do not use: in eyes; over large areas of the body;

If allergic to any of the ingredients; for more than one week unless directed by a physician.

Stop use and consult a doctor:

if the condition persists or gets worse; a rash or other allergic reaction develops

Keep out of reach of children.

If ingested, contact a Poison

Control Center right away.

Directions

Directions: clean affected area; apply small amount of this product (an amount equal to the surface area of the tip of a finger) on the area 1 to 3 times daily; may be covered with a sterile bandage

Other information:

Store at room temperature.

Inactive Ingredient

Vaseline
Mineral Oil
Purified Water

PACKAGE LABEL

Genuine Triple Antibiotic

First Aid Ointment

To Help Prevent Infection

Each Gram Contains:

Bacitracin Zinc 400 units

Neomycin Sulfate 5 mg

(equivalent to 3.5 mg

Neomycin base)

Polymyxin B Sulfate 5000 units

Net Wt. 0.5g ; (1/64 oz)

Manufactured in CHINA for

GENUINE FIRST AID.

Triple Antibiotic Ointment 10pcs

Net wt. 0.9g (1/32oz)

100
Triple Antibiotic